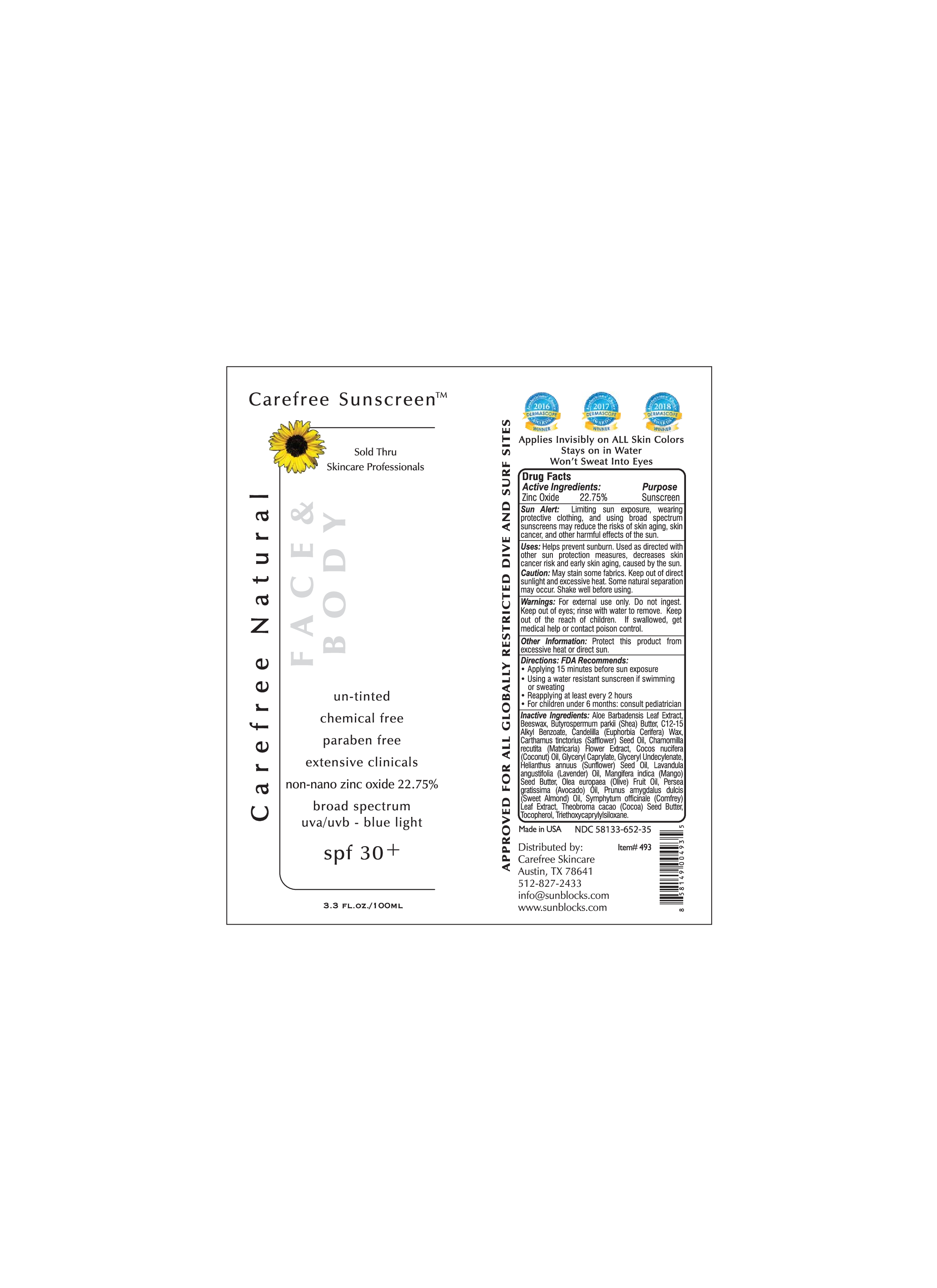 DRUG LABEL: SPF30
NDC: 58133-652 | Form: LOTION
Manufacturer: Cosmetic Specialty Labs, Inc.
Category: otc | Type: HUMAN OTC DRUG LABEL
Date: 20211104

ACTIVE INGREDIENTS: ZINC OXIDE 22.75 g/100 mL
INACTIVE INGREDIENTS: YELLOW WAX; COCONUT OIL; COCOA BUTTER; SAFFLOWER OIL; GLYCERYL 1-UNDECYLENATE; OLIVE OIL; TRIETHOXYCAPRYLYLSILANE; CHAMOMILE; MANGIFERA INDICA SEED BUTTER; .ALPHA.-TOCOPHEROL ACETATE; SHEA BUTTER; AVOCADO OIL; GLYCERYL CAPRYLATE; SUNFLOWER OIL; ALMOND OIL; ALKYL (C12-15) BENZOATE; CANDELILLA WAX; LAVENDER OIL; ALOE VERA LEAF; COMFREY

Active Ingredient

Zinc Oxide

Purpose

Sunscreen

Sun Alert:

Limiting sun exposure, wearing protective clothing, and using broad spectrum sunscreens may reduce the risks of skin aging, skin cancer, and other harmful effects of the sun.

Uses

Helps prevent sunburn. Used as directed with other sun proctection measures, decreases skin cancer risk and early skin aging, caused by the sun.

Caution

Keep out of direct sunlight and excessive heat. Some natural seperation may occur. Shake well before using.

Warnings

For external use only. Do not ingest. Keep out of eyes; rinse with water to remove. Keep out of reach of children. If swallowed, get medical help or contact poison control.

Other Information

Protect this product from excessive heat or direct sun.

Directions: FDA Recommends

- Applying 15 minutes before sun exposure
- Using a water resistant sunscreen if swimming or sweating
- Reapplying at least every 2 hours
- For children under 6 months: consult pediatrician

Inactive Ingredients

Aloe Barbadensis Leaf Extract, Beeswax, Butyrospermum parkii (Shea) Butter, C12-15 Alkyl Benzoate, Candelilla (Euphorbia Cerifera) Wax, Carthamus tinctorius (Safflower) Seed Oil, Chamomilla recutita (Matricaria) Flower Extract, Cocos nucifera (Coconut) Oil, Glyceryl Caprylate, Glyceryl Undecylenate, Helianthus annuus (Sunflower) Seed Oil, Lavandula angustifolia (Lavender) Oil, Mangifera indica (Mango) Seed Butter, Olea europaea (Olive) Fruit Oil, Persea gratissima (Avocado) Oil, Symphytum officinale (Comfrey) Leat Extract, Theobroma cacao (Cocoa) Seed Butter, Tocopherol, Triethoxycaprylylsiloxane